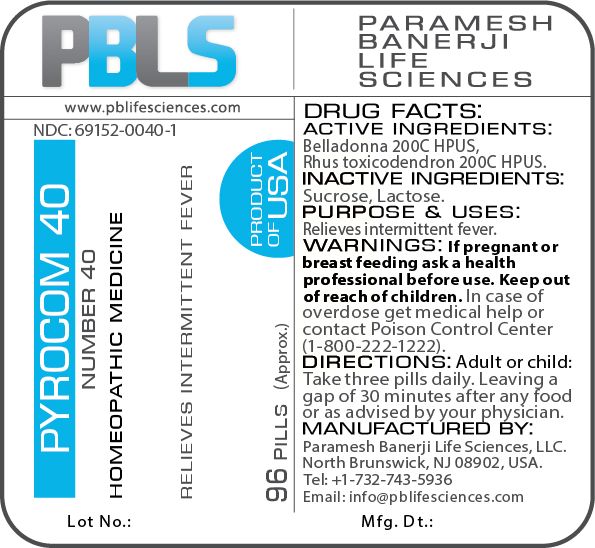 DRUG LABEL: Pyrocom 40 (Number 40)
NDC: 69152-0040 | Form: PELLET
Manufacturer: Paramesh Banerji Life Sciences LLC
Category: homeopathic | Type: HUMAN OTC DRUG LABEL
Date: 20180806

ACTIVE INGREDIENTS: ATROPA BELLADONNA 200 [hp_C]/1 1; TOXICODENDRON PUBESCENS LEAF 200 [hp_C]/1 1
INACTIVE INGREDIENTS: SUCROSE; LACTOSE

DRUG FACTS: Active Ingredients

Belladonna 200C HPUS, Rhus toxicodendron 200C HPUS

Inactive Ingredients

Sucrose, Lactose

Purpose

Relieves intermittent fever

Uses

Relieves intermittent fever

Warnings

If pregnant or breast feeding ask a health professional before use.

Keep out of reach of children. In case of overdose, get medical help or contact a Poison Control Center (1-800-222-1222) right away.

Direction

Adult or child: Take three pills daily. Leaving a gap of 30 minutes after any food or as advised by your physician.

Manufactured by

Paramesh Banerji Life Sciences, LLC.

North Brunswick, NJ 08902, USA.

Tel: +1-732-743-5936

Email: info@pblifesciences.com

Principal Display Panel

NDC: 69152-0040-1

Pyrocom 40

Number 40

Homeopathic Medicine

Relieves intermittent fever

96 Pills (Approx.)

Product of USA